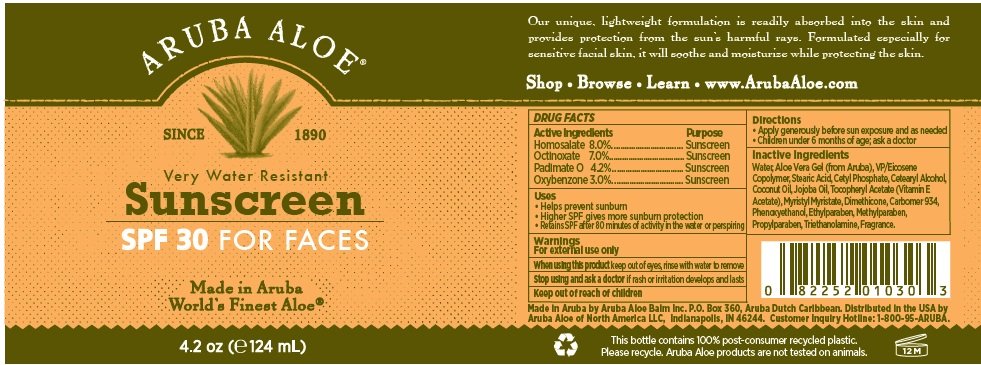 DRUG LABEL: Aruba Aloe Very Water Resistant Sunscreen - For Faces
NDC: 53675-154 | Form: LOTION
Manufacturer: Aruba Aloe Balm NV
Category: otc | Type: HUMAN OTC DRUG LABEL
Date: 20231114

ACTIVE INGREDIENTS: HOMOSALATE 80 mg/1 mL; OCTINOXATE 70 mg/1 mL; PADIMATE O 42 mg/1 mL; OXYBENZONE 30 mg/1 mL
INACTIVE INGREDIENTS: WATER; ALOE VERA LEAF; STEARIC ACID; CETYL PHOSPHATE; CETOSTEARYL ALCOHOL; COCONUT OIL; JOJOBA OIL; ACETATE ION; MYRISTYL MYRISTATE; DIMETHICONE; CARBOMER 934; PHENOXYETHANOL; ETHYLPARABEN; METHYLPARABEN; PROPYLPARABEN; TROLAMINE

Aruba Aloe Very Water Resistant Sunscreen SPF 30 For Faces

Active Ingredients

Homosalate 8.0%

Octinoxate 7.0%

Padimate O 4.2%

Oxybenzone 3.0%

Purpose

Sunscreen

Uses

- Helps prevent sunburn
- Higher SPF gives more sunburn protection
- Retains SPF after 80 minutes of activity in the water or perspiring

Warnings

For external use only.

When using this product

keep out of eyes, rinse with water to remove.

Stop using and ask a doctor

if rash or irritation develops and lasts

Keep out of reach of children

Directions

- Apply generously before sun exposure and as needed
- Children under 6 months of age; ask a doctor.

Inactive Ingredients

Water, Aloe Vera Gel (from Aruba), VP/Eicosene Copolymer, Stearic Acid, Cetyl Phosphate, Cetearyl Alcohol, Coconut Oil, Jojoba Oil, Tocopheryl Acetate (Vitamin E Acetate), Myristyl Myristate, Dimethicone, Carbomer 934, Phenoxyethanol, Ethylparaben, Methylparaben, Propylparaben, Triethanolamine, Fragrance

PACKAGE LABEL

Aruba Aloe

Since 1890

Very Water Resistant

Sunscreen

SPF 30 FOR FACES

Made In Aruba

World's Finest Aloe

4.2oz (e124mL)

Our unique, lightweight formulation is readily absorbed into the skin and provides protection from the suns harmful rays. Formulated especially for sensitive facial skin, it will soothe and moisturize while protecting the skin.

Shop. Browse, Learn. Www. ArubaAloe.com

This bottle contains 100% post consumer recycled plastic. Please recycle. Aruba Aloe products are not tested on animals.